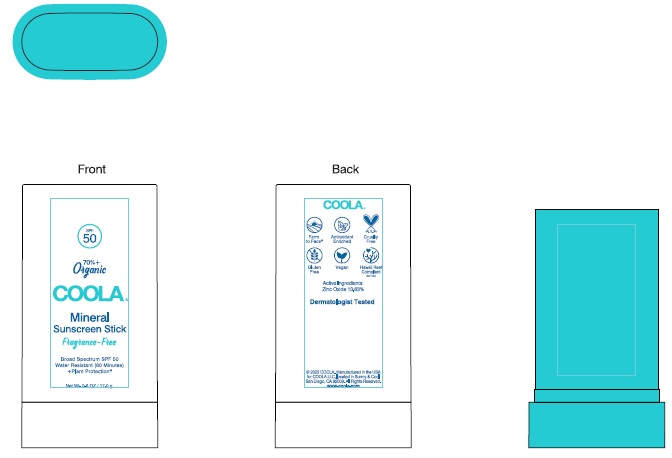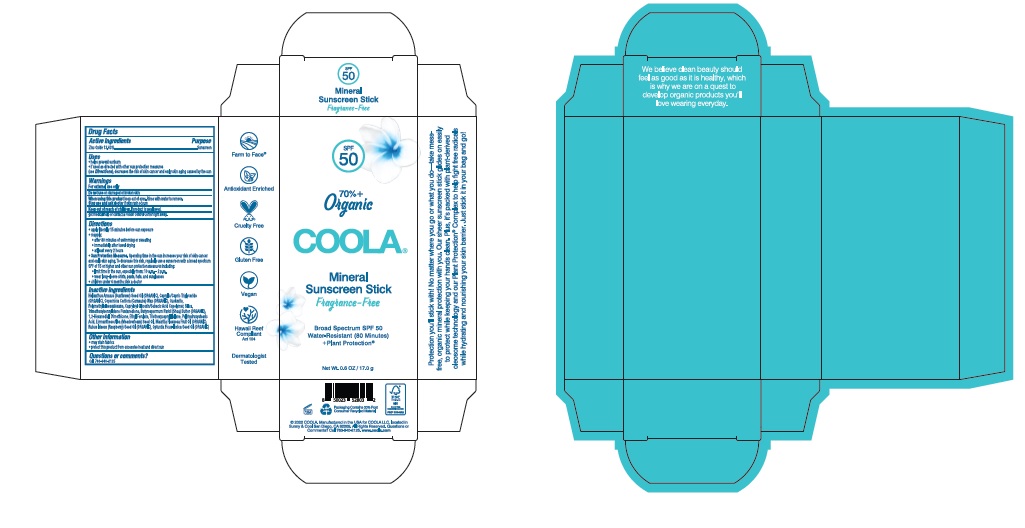 DRUG LABEL: Mineral Sunscreen Stick SPF 50

NDC: 79753-032 | Form: STICK
Manufacturer: COOLA LLC
Category: otc | Type: HUMAN OTC DRUG LABEL
Date: 20251214

ACTIVE INGREDIENTS: ZINC OXIDE 13.63 g/100 g
INACTIVE INGREDIENTS: SUNFLOWER OIL; MEDIUM-CHAIN TRIGLYCERIDES; CARNAUBA WAX; CERESIN; POLYMETHYLSILSESQUIOXANE (11 MICRONS); CAPRYLOYL GLYCERIN/SEBACIC ACID COPOLYMER (2000 MPA.S); SILICON DIOXIDE; TRIMETHOXYBENZYLIDENE PENTANEDIONE; SHEA BUTTER; 1,2-HEXANEDIOL; DIMETHICONE; ETHYL FERULATE; TRIETHOXYCAPRYLYLSILANE; POLYHYDROXYSTEARIC ACID (2300 MW); MEADOWFOAM SEED OIL; MAURITIA FLEXUOSA FRUIT OIL; RASPBERRY SEED OIL; OPUNTIA FICUS-INDICA WHOLE

COOLA Mineral Sunscreen Stick SPF 50

Drug Facts

Active Ingredients

Zinc Oxide 13.63%

Purpose

Suncreen

Uses

- helps prevent sunburn

- if used as directed with other sun protection measures

(see Directions), decreases the risk of skin cancer and early skin aging caused by the sun

Warnings

For external use only

Do not useon damaged or broken skin

When using this productkeep out of eyes. Rinse with water to remove.

Stop use and ask doctorif skin rash occurs

Keep out of reach of children.If product is swallowed, get

medical help or contact a Poison Control Center right away.

Directions
• apply liberally 15 minutes before sun exposure.
• reapply:
● after 80 minutes of swimming or sweating
● immediately after towel drying
● at least every 2 hours
Sun Protection Measures.Spending time in the sun increases your risk of skin cancer
and early skin aging. To decrease this risk, regularly use a sunscreen with a broad spectrum
SPF of 15 or higher and other sun protection measures including:
● limit time in the sun, especially from: 10 a.m. - 2 p.m.
● wear long-sleeve shirts, pants, hats, and sunglasses
●Children under 6 months: Ask a doctor

Inactive Ingredients
Helianthus Annus (Sunflower) Seed Oil (ORGANIC), caprylic/Capric Triglyceride
(ORGANIC), Copernicia Cerifera (Carnauba) Wax (ORGANIC), Ozokerite,
Polymethylsilsesquioxane, Capryloyl Glycerin/Sebacic Acid Copolymer, Silica,
Trimethoxybenzylidene Pentanedione, Butyrospermum Parkii (Shea) Butter (ORGANIC),
1,2-Heanediol Dimethicone, Ethyl Ferulate, Triethoxycaprylylsilane, Polyhydroxystearic
Acid, Limnanthese Alba (Meadowfoam) Seed Oil, Mauritia Flexuosa Fruit Oil (ORGANIC),
Rubus Idaeus (Raspberry) Seed Oil (ORGANIC), Optuntia Ficus-Indica Seed Oil (ORGANIC)

Other information

- may stain fabrics
- protect this product from excessive heat and direct sun

Questions or comments?
Call 760-940-2125

COOLA Label

SPF

50

70%+

Organic

COOLA®

Classic

Sunscreen Stick

Fragrance-Free

Broad Spectrum SPF 50

Water-Resistant (80 Minutes)

+Plant Protection®

Net Wt. 0.6 OZ / 17.0 g

©2022 COOLA. Manufactured in the USA for COOLA, located in

Sunny & Cool San Diego, CA 92010. All Rights Reserved. Questions or

Comments? Call 760-940-2125. www.coola.com

res